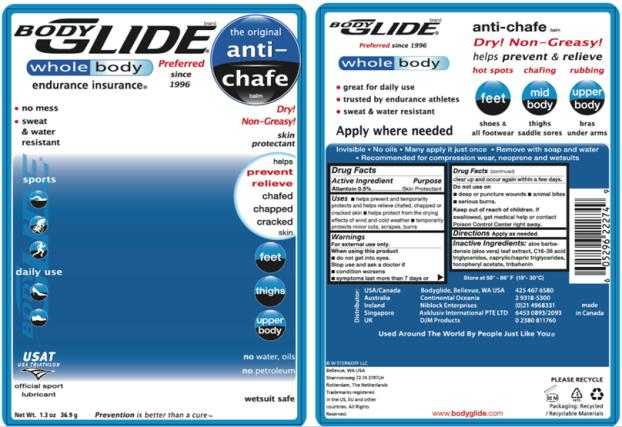 DRUG LABEL: Bodyglide anti chafe balm
NDC: 15197-007 | Form: STICK
Manufacturer: W STERNOFF LLC
Category: otc | Type: HUMAN OTC DRUG LABEL
Date: 20091210

ACTIVE INGREDIENTS: ALLANTOIN 5 mg/1 g
INACTIVE INGREDIENTS: ALOE; .ALPHA.-TOCOPHEROL ACETATE, D-; TRIBEHENIN; MEDIUM-CHAIN TRIGLYCERIDES; FD&C RED NO. 40

Anti-chafe balm

Active Ingredient:

Allantoin 0.5%

Purpose

Skin Protectant

Uses

- helps prevent and helps relieve chafed, chapped or cracked skin
- helps protect from the drying effects of wind and cold weather

Warnings

For external use only.

When using this product

- do not get into eyes

Stop use and ask a doctor if

- condition worsens
- symptoms last more than 7 days or clear up and occur again within a few days

Do not use on

- deep or puncture wounds
- animal bites
- serious burns

Keep out of reach of children. If swallowed, get medical help or contact Poison Control Center right away.

Directions

Apply as needed.

Inactive Ingredients

aloe barbadensis extract, C18-36 acid triglycerides, caprylic/capric triglycerides, FD & C Red No. 40, tocopheryl acetate, tribehenin

Questions +1 425.467.6580

Distributor: Bodyglide, Bellevue, WA USA

©2009 W Sternoff LLC, Bellevue, WA USA

All rights reserved www.bodyglide.com
Trademarks registered

Made in Canada

Principal Display Panel

BODYGLIDE
anti-chafe balm

Dry, Non-Greasy

helps prevent & relieve

hot spots, chafing, rubbing

feet, mid body, upper body

shoes & all footwear, thighs, saddle sores, bras, under arms
great for daily use

trusted by endurance athletes

sweat & water resistant

Invisible, No Oils, Many apply it just once, Remove with soap and water, Recommended for compression wear, neoprene and wetsuits